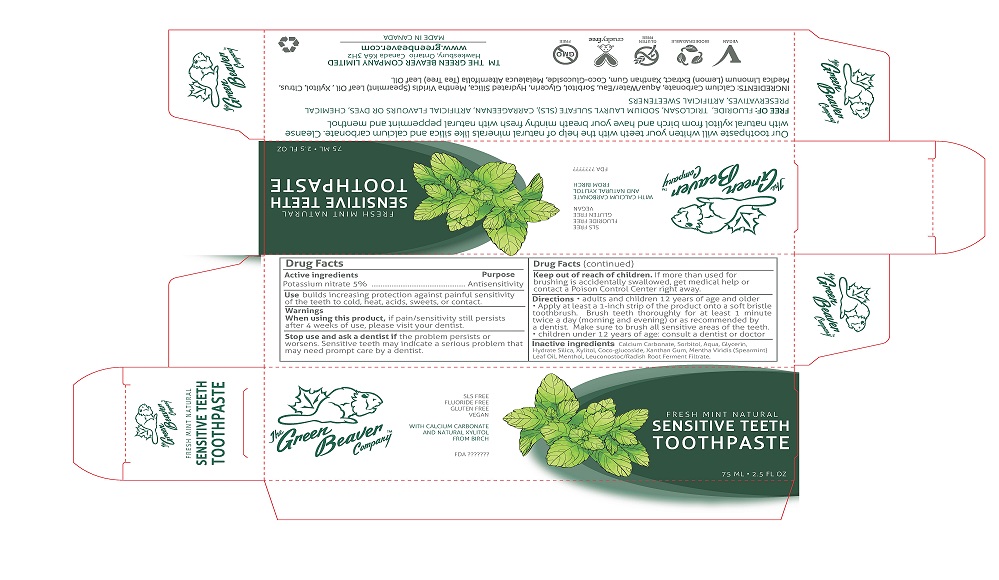 DRUG LABEL: Sensitive Teeth
NDC: 76098-001 | Form: PASTE
Manufacturer: The Green Beaver Company Ltd.
Category: otc | Type: HUMAN OTC DRUG LABEL
Date: 20170810

ACTIVE INGREDIENTS: POTASSIUM NITRATE 5 g/100 mL
INACTIVE INGREDIENTS: LEUCONOSTOC/RADISH ROOT FERMENT FILTRATE; COCO GLUCOSIDE; CALCIUM CARBONATE; SORBITOL; XYLITOL; GLYCERIN; WATER; HYDRATED SILICA; XANTHAN GUM; MENTHA SPICATA; MENTHOL

Active ingredients

Postassium nitrate, 5%

Purpose

Antisensitivity

Keep out of reach of children. If more than used for brushing is accidentally swallowed, get medical help or contact a Poison Control Center right away

INDICATIONS AND USAGE

Use builds increasing protection against painful sensitivity of the teeth to cold, acids, sweets, or contact

Warnings

When using this product, if pain/sensitivity still persists after 4 weeks or use, please visit your dentist

Directions

- adults and children 12 years of age and older
- Apply at least a 1-inch strip of the product onto soft bristle toothbrush
- Brush teeth thoroughly for at least 1 minute twice a day (morning and evening) or as recommended by a dentist
- Make sure to brush all sensitive areas of the teeth
- Children under 12 years of age: consult a dentist or doctor

Inactive ingredients

Calcium carbonate, Sorbitol, Agua, Glycerin, Hydrate Silica, Xynthol, Coco-glucoside, Xanthan Gum, Mentha Viridis (Spearmint) Leaf Oil, Menthol, Leuconostoc/Radish Root Ferment Filtrate